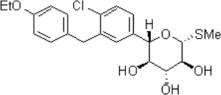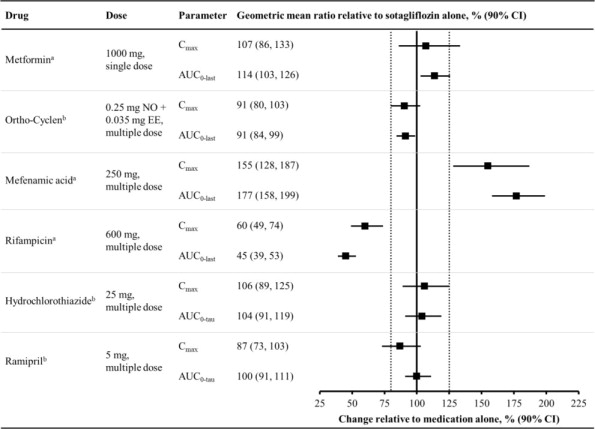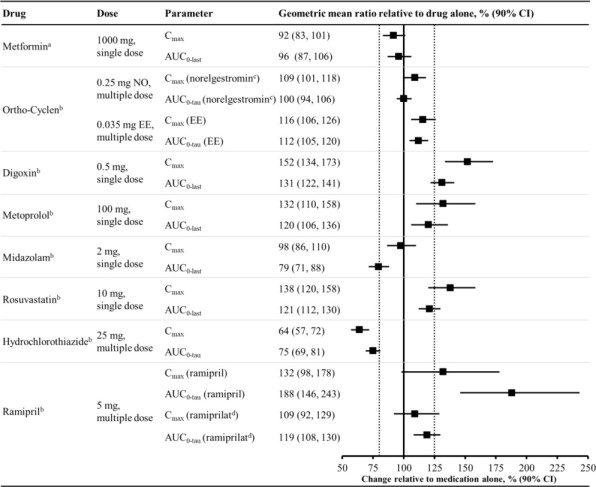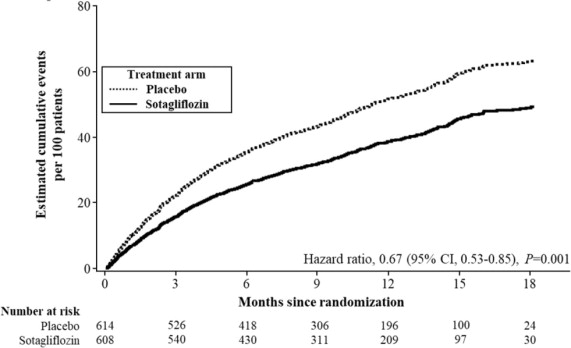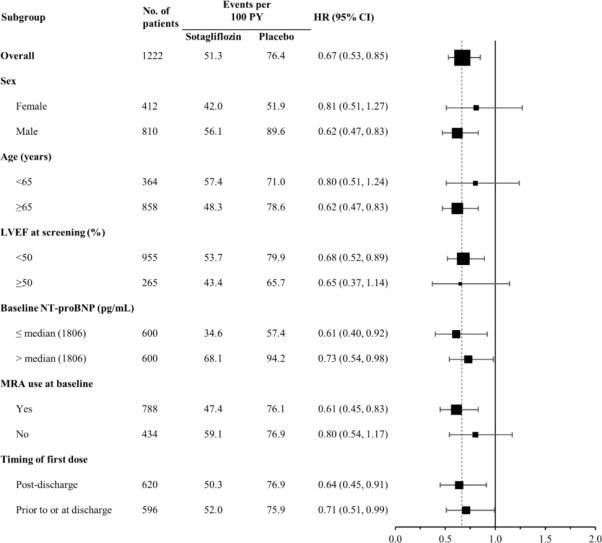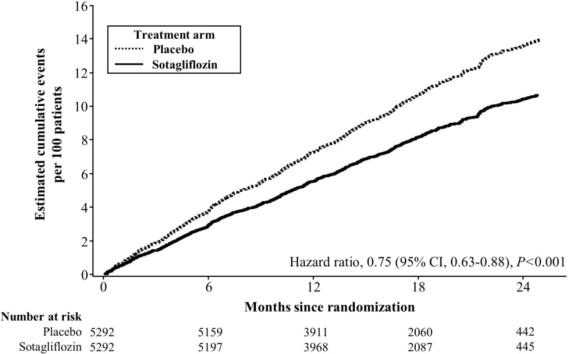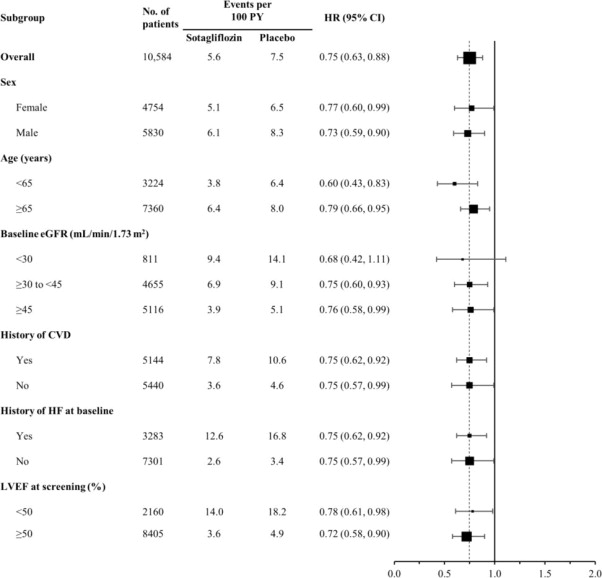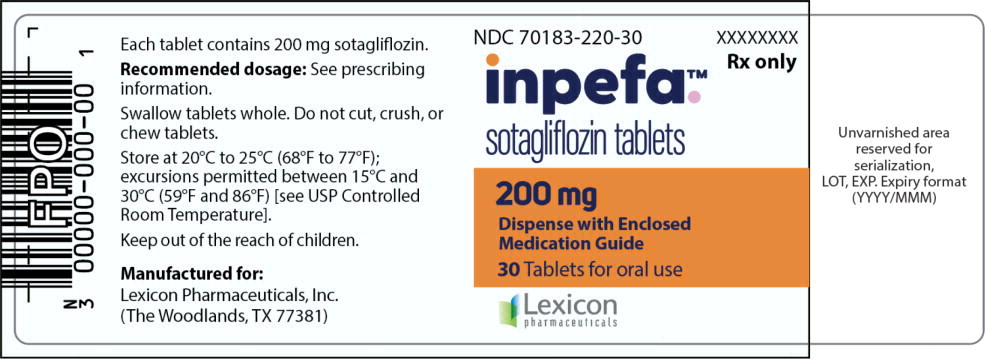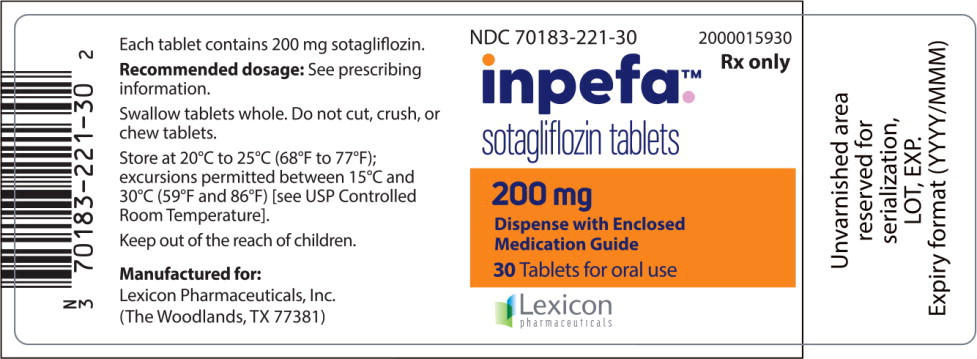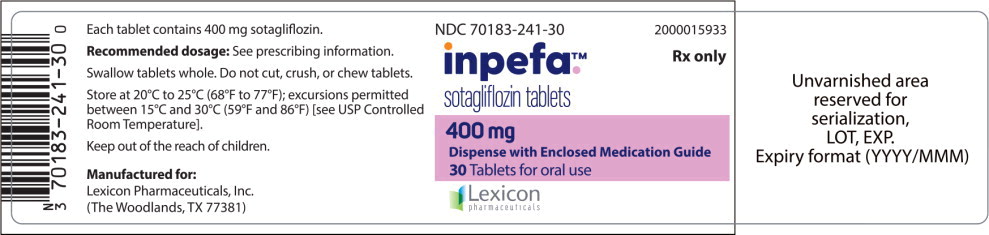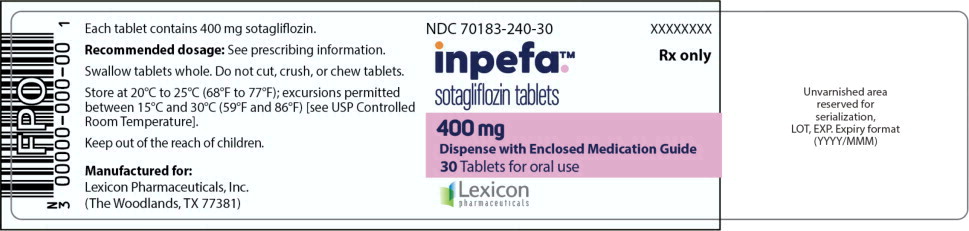 DRUG LABEL: INPEFA
NDC: 70183-220 | Form: TABLET
Manufacturer: Lexicon Pharmaceuticals, Inc.
Category: prescription | Type: HUMAN PRESCRIPTION DRUG LABEL
Date: 20260129

ACTIVE INGREDIENTS: sotagliflozin 200 mg/1 1
INACTIVE INGREDIENTS: Microcrystalline cellulose 102; Microcrystalline cellulose 200; Croscarmellose sodium; silicon dioxide; Talc; Magnesium stearate; polyvinyl alcohol, unspecified; polyethylene glycol, unspecified; titanium dioxide; FD&C Blue No. 2

HIGHLIGHTS OF PRESCRIBING INFORMATION

These highlights do not include all the information needed to use INPEFA safely and effectively. See full prescribing information for INPEFA.
INPEFA® (sotagliflozin) tablets, for oral use
Initial U.S. Approval: 2023

1 INDICATIONS AND USAGE

INPEFA is a sodium-glucose cotransporter 2 (SGLT2) inhibitor indicated to reduce the risk of cardiovascular death, hospitalization for heart failure, and urgent heart failure visit in adults with:

- heart failure (1) or
- type 2 diabetes mellitus, chronic kidney disease, and other cardiovascular risk factors (1)

2 DOSAGE AND ADMINISTRATION

Correct volume status before starting INPEFA at 200 mg daily and titrate to 400 mg as tolerated. (2.2) In patients with decompensated heart failure, begin dosing when patients are hemodynamically stable. (2.1)

Withhold INPEFA at least 3 days, if possible, prior to major surgery or procedures associated with prolonged fasting. (2.3)

3 DOSAGE FORMS AND STRENGTHS

Tablets: 200 mg and 400 mg (3)

4 CONTRAINDICATIONS

- History of serious hypersensitivity reaction to INPEFA. (4)

5 WARNINGS AND PRECAUTIONS

- Diabetic Ketoacidosis in Patients with Type 1 Diabetes Mellitus and Other Ketoacidosis: Consider ketone monitoring in patients with type 1 diabetes mellitus and consider ketone monitoring in others at risk for ketoacidosis, as indicated. Assess for ketoacidosis regardless of presenting blood glucose levels and discontinue INPEFA if ketoacidosis is suspected. Monitor patients for resolution of ketoacidosis before restarting. (5.1)
- Volume Depletion: Before initiating, correct volume status. Monitor for signs and symptoms of hypotension during therapy. (5.2)
- Urosepsis and Pyelonephritis: Monitor for signs and symptoms during therapy and treat promptly. (5.3)
- Hypoglycemia with Concomitant Use with Insulin and Insulin Secretagogues: Lower dose of insulin or insulin secretagogue may be required. (5.4)
- Necrotizing Fasciitis of the Perineum (Fournier's Gangrene): Monitor for pain, tenderness, erythema, or swelling in the genital or perineal area, along with fever or malaise. Discontinue INPEFA and treat urgently. (5.5)
- Genital Mycotic Infections: Monitor and treat as appropriate. (5.6)

6 ADVERSE REACTIONS

Most common adverse reactions (incidence ≥ 5%) are urinary tract infection, volume depletion, diarrhea, and hypoglycemia. (6.1)

To report SUSPECTED ADVERSE REACTIONS, contact Lexicon at 1-855-330-2573 or FDA at 1-800-FDA-1088 or www.fda.gov/medwatch.

7 DRUG INTERACTIONS

Digoxin: Monitor digoxin levels. (7.1)

Uridine 5'-diphospho-glucuronosyltransferase Inducers (e.g., rifampin): Sotagliflozin exposure is reduced. Consider monitoring of clinical status. (7.2)

Lithium: Monitor serum lithium concentrations. (7.3)

8 USE IN SPECIFIC POPULATIONS

Pregnancy: Advise females of the potential risk to a fetus especially during the second and third trimesters. (8.1)

Lactation: INPEFA is not recommended when breastfeeding. (8.2)

Geriatrics: Higher incidence of adverse reactions related to volume depletion. (5.2, 8.5)

Renal Impairment: Higher incidence of adverse reactions related to volume depletion. (5.2, 8.6)

FULL PRESCRIBING INFORMATION

1 INDICATIONS AND USAGE

INPEFA is indicated to reduce the risk of cardiovascular death, hospitalization for heart failure, and urgent heart failure visit in adults with:

- heart failure or
- type 2 diabetes mellitus, chronic kidney disease, and other cardiovascular risk factors

2 DOSAGE AND ADMINISTRATION

2.1 Prior to Initiation of INPEFA

Assess volume status and, if necessary, correct volume depletion prior to initiation of INPEFA [see Warnings and Precautions (5.2) and Use in Specific Populations (8.5, 8.6)].

Assess renal function prior to initiation of INPEFA and then as clinically indicated [see Warnings and Precautions (5.2)].

For patients with decompensated heart failure, dosing may begin as soon as the patient is hemodynamically stable, including during hospitalization or urgent outpatient treatment or immediately upon discharge.

2.2 Recommended Dosage

The recommended starting dose of INPEFA is 200 mg orally once daily not more than one hour before the first meal of the day.

Up-titrate after at least 2 weeks to 400 mg orally once daily as tolerated [see Clinical Studies (14)]. Down-titrate to 200 mg as necessary [see Adverse Reactions (6.1), Warnings and Precautions (5) and Use in Specific Populations (8.6)].

Swallow tablets whole. Do not cut, crush, or chew tablets.

If a dose of INPEFA is missed by more than 6 hours, take the next dose as prescribed the next day.

2.3 Temporary Interruption for Surgery

Withhold INPEFA at least 3 days, if possible, prior to major surgery or procedures associated with prolonged fasting. Resume INPEFA when the patient is clinically stable and has resumed oral intake [see Warnings and Precautions (5.1) and Clinical Pharmacology (12.3)].

3 DOSAGE FORMS AND STRENGTHS

INPEFA 200 mg printed tablet is an oval, blue, film-coated tablet imprinted in black ink with “LX200” on one side.

INPEFA 200 mg debossed tablet is an oval, blue, film-coated tablet debossed with “LEX” on one side and “200” on the other side.

INPEFA 400 mg debossed tablet is an oval, yellow, film-coated tablet debossed with “LEX” on one side and “400” on the other side.

4 CONTRAINDICATIONS

INPEFA is contraindicated in patients with a history of serious hypersensitivity reaction to INPEFA.

5 WARNINGS AND PRECAUTIONS

5.1 Diabetic Ketoacidosis in Patients with Type 1 Diabetes Mellitus and Other Ketoacidosis

In patients with type 1 diabetes mellitus, INPEFA significantly increases the risk of diabetic ketoacidosis, a life-threatening event, beyond the background rate. In placebo-controlled trials of patients with type 1 diabetes mellitus, the risk of ketoacidosis was markedly increased in patients who received sodium glucose cotransporter 2 (SGLT2) inhibitors compared to patients who received placebo; this risk may be greater with higher doses of INPEFA. INPEFA is not indicated for glycemic control.

Type 2 diabetes mellitus and pancreatic disorders (e.g., history of pancreatitis or pancreatic surgery) are also risk factors for ketoacidosis. There have been postmarketing reports of fatal events of ketoacidosis in patients with type 2 diabetes using SGLT2 inhibitors.

Precipitating conditions for diabetic ketoacidosis or other ketoacidosis include acute febrile illness, reduced caloric intake, ketogenic diet, surgery, insulin dose reduction, volume depletion, and alcohol abuse.

Signs and symptoms are consistent with dehydration and severe metabolic acidosis and include nausea, vomiting, abdominal pain, generalized malaise, and shortness of breath. Blood glucose levels at presentation may be below those typically expected for diabetic ketoacidosis (e.g., less than 250 mg/dL). Ketoacidosis and glucosuria may persist longer than typically expected. Urinary glucose excretion persists for 3 days after discontinuing INPEFA [see Clinical Pharmacology (12.3)]; however, there have been postmarketing reports of ketoacidosis and glucosuria lasting greater than 6 days and some up to 2 weeks after discontinuation of SGLT2 inhibitors.

Consider ketone monitoring in patients with type 1 diabetes mellitus and consider ketone monitoring in others at risk for ketoacidosis if indicated by the clinical situation. Assess for ketoacidosis regardless of presenting blood glucose levels in patients who present with signs and symptoms consistent with severe metabolic acidosis. If ketoacidosis is suspected, discontinue INPEFA, promptly evaluate, and treat ketoacidosis, if confirmed. Monitor patients for resolution of ketoacidosis before restarting INPEFA.

Withhold INPEFA, if possible, in temporary clinical situations that could predispose patients to ketoacidosis. Resume INPEFA when the patient is clinically stable and has resumed oral intake [see Dosage and Administration (2.3)].

Educate all patients on the signs and symptoms of ketoacidosis and instruct patients to discontinue INPEFA and seek medical attention immediately if signs and symptoms occur.

5.2 Volume Depletion

INPEFA can cause intravascular volume depletion which may sometimes manifest as symptomatic hypotension or acute transient changes in creatinine. There have been postmarketing reports of acute kidney injury, some requiring hospitalization and dialysis, in patients with type 2 diabetes mellitus receiving SGLT2 inhibitors. Patients with impaired renal function (eGFR < 60 mL/min/1.73 m^2), elderly patients, or patients on loop diuretics may be at increased risk for volume depletion or hypotension [see Adverse Reactions (6.1) and Use in Specific Populations (8.5, 8.6)]. Before initiating INPEFA in patients with one or more of these characteristics, assess volume status and renal function. Monitor for signs and symptoms of hypotension, and renal function after initiating therapy.

5.3 Urosepsis and Pyelonephritis

Treatment with SGLT2 inhibitors, including INPEFA, increases the risk for urinary tract infections. Serious urinary tract infections including urosepsis and pyelonephritis requiring hospitalization have been reported. Evaluate patients for signs and symptoms of urinary tract infections and treat promptly, if indicated [see Adverse Reactions (6.1)].

5.4 Hypoglycemia with Concomitant Use with Insulin and Insulin Secretagogues

Insulin and insulin secretagogues are known to cause hypoglycemia. INPEFA may increase the risk of hypoglycemia when combined with insulin or an insulin secretagogue [see Adverse Reactions (6.1)]. Therefore, a lower dose of insulin or insulin secretagogue may be required to minimize the risk of hypoglycemia when these agents are used in combination with INPEFA.

5.5 Necrotizing Fasciitis of the Perineum (Fournier's Gangrene)

Reports of necrotizing fasciitis of the perineum (Fournier's Gangrene), a rare but serious and life-threatening necrotizing infection requiring urgent surgical intervention, have been identified in postmarketing surveillance in patients with diabetes mellitus receiving SGLT2 inhibitors. Cases have been reported in both females and males. Serious outcomes have included hospitalization, multiple surgeries, and death.

Patients treated with INPEFA presenting with pain, tenderness, erythema, or swelling in the genital or perineal area, along with fever or malaise, should be assessed for necrotizing fasciitis. If suspected, start treatment immediately with broad-spectrum antibiotics and, if necessary, surgical debridement. Discontinue INPEFA, closely monitor blood glucose levels, and provide appropriate alternative therapy for heart failure.

5.6 Genital Mycotic Infections

INPEFA increases the risk of genital mycotic infections. Patients with a history of genital mycotic infections were more likely to develop genital mycotic infections [see Adverse Reactions (6.1)]. Monitor and treat appropriately.

5.7 Positive Urine Glucose Test

Monitoring glucose levels with urine glucose tests is not recommended as SGLT2 inhibition increases urinary glucose excretion and will lead to positive urine glucose tests. Use alternative methods to monitor glucose levels.

5.8 Interference with 1,5-anhydroglucitol (1,5-AG) Assay

Monitoring glucose levels with 1,5-AG assay is not recommended as measurements of 1,5-AG are unreliable in assessing glucose levels in patients taking SGLT2 inhibitors. Use alternative methods to monitor glucose levels.

6 ADVERSE REACTIONS

The following important adverse reactions are described elsewhere in the labeling:

- Diabetic Ketoacidosis in Patients with Type 1 Diabetes Mellitus and Other Ketoacidosis [see Warnings and Precautions (5.1)]
- Volume Depletion [see Warnings and Precautions (5.2)]
- Urosepsis and Pyelonephritis [see Warnings and Precautions (5.3)]
- Hypoglycemia with Concomitant Use with Insulin and Insulin Secretagogues [see Warnings and Precautions (5.4)]
- Necrotizing Fasciitis of the Perineum (Fournier's Gangrene) [see Warnings and Precautions (5.5)]
- Genital Mycotic Infections [see Warnings and Precautions (5.6)]

6.1 Clinical Trials Experience

Because clinical trials are conducted under widely varying conditions, adverse reaction rates observed in the clinical trials of a drug cannot be directly compared to rates in the clinical trials of another drug and may not reflect the rates observed in clinical practice.

In the phase 3 (SOLOIST [see Clinical Studies (14.1)] and SCORED [see Clinical Studies (14.2)]) placebo-controlled trials, 5,896 subjects received INPEFA.

In the SOLOIST study, 336 patients (56%) reached the 400 mg dose. In the SCORED study, 3,934 patients (74%) reached the 400 mg dose.

In the SOLOIST study, 5.6% of patients in the INPEFA group and 5.4% of patients in the placebo group discontinued therapy due to adverse events (AEs). In the SCORED study, 5.0% of patients in the INPEFA group and 4.5% of patients in the placebo group discontinued therapy due to AEs.

Table 1 Adverse Reactions Reported in ≥ 2% of Patients Treated with INPEFA and Greater Than Placebo in Either SOLOIST or SCORED
Adverse Reaction | SOLOIST N = 1,216 |  | SCORED N = 10,577
Adverse Reaction | Placebo (%) N = 611 | INPEFA (%) N = 605 | Placebo (%) N = 5,286 | INPEFA (%) N = 5,291
Urinary tract infection | 7.2 | 8.6 | 11.0 | 11.5
Volume depletion | 8.8 | 9.3 | 4.0 | 5.2
Diarrhea | 4.1 | 6.9 | 6.0 | 8.4
Hypoglycemia | 2.8 | 4.3 | 7.9 | 7.7
Dizziness | 2.5 | 2.6 | 2.8 | 3.3
Genital mycotic infection | 0.2 | 0.8 | 0.9 | 2.4

Changes in Laboratory Test Values During Treatment

Increase in Serum Creatinine and Decrease in eGFR

Initiation of SGLT2 inhibitors, including INPEFA, causes a small increase in serum creatinine and decrease in eGFR. These changes in serum creatinine and eGFR generally occur within 4 weeks of starting therapy and then stabilize regardless of baseline kidney function. Changes that do not fit this pattern should prompt further evaluation to exclude the possibility of acute kidney injury. In studies that included patients with type 2 diabetes mellitus with moderate renal impairment, the acute effect on eGFR reversed after treatment discontinuation, suggesting acute hemodynamic changes may play a role in the renal function changes observed with INPEFA [see Warnings and Precautions (5.2) and Use in Specific Populations (8.6)].

7 DRUG INTERACTIONS

7.1 Digoxin

There is an increase in the exposure of digoxin when coadministered with INPEFA 400 mg. Patients taking INPEFA with concomitant digoxin should be monitored appropriately [see Clinical Pharmacology (12.3)].

7.2 Uridine 5'-diphospho-glucuronosyltransferase (UGT) Inducer

Glucuronidation by UGT1A9, to form the 3-O-glucuronide, was identified as a major metabolic pathway for sotagliflozin. The coadministration of rifampicin, an inducer of UGTs, with a single dose of 400 mg sotagliflozin resulted in a decrease in the exposure to sotagliflozin. This decrease in exposure to sotagliflozin may decrease efficacy [see Clinical Pharmacology (12.3)].

7.3 Lithium

Concomitant use of an SGLT2 inhibitor with lithium may decrease serum lithium concentrations. Monitor serum lithium concentration more frequently during INPEFA initiation and dosage changes.

8 USE IN SPECIFIC POPULATIONS

8.1 Pregnancy

Risk Summary

Based on animal data showing renal effects, INPEFA is not recommended during the second and third trimesters of pregnancy.

Available data with INPEFA in pregnant women are insufficient to evaluate for a drug-associated risk of major birth defects, miscarriage, or other adverse maternal or fetal outcomes. There are risks to the mother and fetus associated with untreated heart failure in pregnancy [see Clinical Considerations].

In rats, renal changes were observed when sotagliflozin was administered during a period of renal development corresponding to the late second and third trimesters of human pregnancy. Exposure approximately 5 times the clinical exposure at the maximum recommended human dose (MRHD) of 400 mg once daily caused increased kidney weights and renal pelvis and tubule dilatations that were partially reversible [see Data].

The estimated background risk of major birth defects and miscarriage for the indicated population is unknown. All pregnancies have a background risk of birth defect, loss or other adverse outcomes. In the U.S. general population, the estimated background risk of major birth defects and miscarriage in clinically recognized pregnancies is 2% to 4% and 15% to 20%, respectively.

Clinical Considerations

Disease-associated Maternal and/or Embryo-fetal Risk

Pregnant women with congestive heart failure are at increased risk for preterm birth. Clinical classification of heart disease may worsen with pregnancy and lead to maternal death.

Data

Animal Data

In embryo-fetal development studies in rats and rabbits, sotagliflozin was administered for intervals coinciding with the first trimester period of organogenesis in humans.

Sotagliflozin was not teratogenic when administered at doses up to 100 mg/kg/day in pregnant rats during embryonic organogenesis (40 times the human exposure at the MRHD). Higher exposures (350 mg/kg or 161 times the human exposure at the MRHD) resulted in embryo-lethality, effects on fetal growth, and cardiovascular and skeletal fetal abnormalities commensurate with maternal toxicity.

Sotagliflozin was not teratogenic when administered at doses up to 200 mg/kg/day in pregnant rabbits (9 times the human exposure at the MRHD).

In a prenatal and postnatal development study in pregnant and lactating rats, sotagliflozin was administered at oral doses up to 100 mg/kg/day from gestation Day 6 through to lactation Day 20 (weaning). An increased incidence of dilated kidneys with discoloration and dilated ureters was observed at doses ≥ 30 mg/kg (≥ 4 times the human exposure at the MRHD). Sotagliflozin did not adversely affect developmental landmarks, sexual maturation, or reproductive performance of the offspring at doses up to 40 times the human exposure at the MRHD.

Sotagliflozin dosed directly to juvenile rats from postnatal Day (PND) 21 until PND 90 at doses of 3, 10, 30, and 75 mg/kg/day caused dose-related increased kidney weights for males given ≥ 10 mg/kg/day and females given ≥ 30 mg/kg/day and was correlated with renal tubular and pelvis dilation for animals given ≥ 30 mg/kg/day. These findings were fully or partially reversed after a 29-day recovery period. These outcomes occurred with drug exposure during periods of renal development in rats that correspond to the late second and third trimesters of human development.

8.2 Lactation

Risk Summary

There are no data on the presence of INPEFA in human milk, the effects on the breastfed infant, or the effects on milk production. Sotagliflozin is present in rat milk (see Data). When a drug is present in animal milk, it is likely to be present in human milk. Since human kidney maturation occurs in utero and during the first 2 years of life when lactational exposure may occur, there may be risk to the developing human kidney.

Because of the potential for serious adverse reactions in a breastfed infant, advise women that breastfeeding is not recommended while taking INPEFA.

Data

In rats, after a single oral dose of radiolabeled sotagliflozin to dams on gestation Day 13 or 18, low to moderate levels of radioactivity were present in fetal tissues. In rat milk, the mean milk/plasma concentration ratios ranged from 0.5 to 2. Exposure to radioactivity was approximately 30% greater in milk than in plasma based on AUC0-inf values.

8.4 Pediatric Use

The safety and effectiveness of INPEFA in pediatric patients under 18 years of age have not been established.

8.5 Geriatric Use

No INPEFA dosage change is recommended based on age.

In the SOLOIST study, a total of 241 (40%) patients treated with INPEFA were between 65 and < 75 years of age, and 174 (29%) were ≥ 75 years of age. In the SCORED study, a total of 2,470 (47%) patients treated with INPEFA were between 65 and < 75 years of age, and 1,240 (23%) were ≥ 75 years of age.

No overall differences in efficacy were detected between these patients and younger patients, and other reported clinical experience has not identified differences in responses between the elderly and younger patients, but greater sensitivity of some older individuals cannot be ruled out.

Elderly patients may be at increased risk for volume depletion adverse reactions, including hypotension. In patients ≥ 65 years of age, a higher proportion of patients treated with INPEFA had adverse reactions of volume depletion [see Warnings and Precautions (5.2) and Adverse Reactions (6.1)].

8.6 Renal Impairment

INPEFA was evaluated in 5,292 patients with chronic kidney disease (eGFR 25 to 60 mL/min/1.73 m^2) in the SCORED study and in 426 patients with heart failure with eGFR < 60 mL/min/1.73 m^2 in the SOLOIST study. The safety profile of INPEFA across eGFR subgroups in these studies was consistent with the known safety profile. There was an increase in volume-related adverse events (e.g., hypotension, dizziness) in patients with eGFR < 30 mL/min/1.73 m^2 relative to the overall safety population [see Warnings and Precautions (5.2) and Adverse Reactions (6.1)].

Efficacy and safety studies with INPEFA did not enroll patients with an eGFR less than 25 mL/min/1.73 m^2 or on dialysis. After starting therapy in these studies, patients were discontinued if eGFR fell below 15 mL/min/1.73 m^2 or were initiated on chronic dialysis.

8.7 Hepatic Impairment

In a clinical pharmacology study in patients with hepatic impairment, the exposure in mild hepatic impairment was not increased, but was approximately 3-fold as high in moderate and approximately 6-fold as high in severely hepatic-impaired subjects compared to subjects with normal hepatic function [see Clinical Pharmacology (12.3)].

No dosage adjustment is necessary in patients with mild hepatic impairment.

The safety and efficacy of INPEFA have not been established in patients with moderate or severe hepatic impairment [see Clinical Pharmacology (12.3)]. INPEFA is not recommended in patients with moderate or severe hepatic impairment.

10 OVERDOSAGE

There were no confirmed reports of symptomatic overdose with sotagliflozin during the clinical development program of INPEFA.

In the event of an overdose with INPEFA, contact the Poison Control Center. Employ the usual supportive measures as dictated by the patient's clinical status.

The removal of sotagliflozin by hemodialysis has not been studied.

11 DESCRIPTION

INPEFA tablets for oral administration contain sotagliflozin, a sodium-glucose cotransporter 2 (SGLT2) inhibitor.

The chemical name of sotagliflozin is (2S,3R,4R,5S,6R)-2-(4-chloro-3-(4-ethoxybenzyl)phenyl)-6-(methylthio)tetrahydro-2H-pyran-3,4,5-triol.

Its molecular formula is C21H25ClO5S and the molecular weight is 424.94. The structural formula is:

Sotagliflozin is a white to off-white solid. It is practically insoluble in water.

Each film-coated tablet of INPEFA contains 200 mg or 400 mg of sotagliflozin and the following inactive ingredients. The core of the tablet contains colloidal silicon dioxide, croscarmellose sodium, magnesium stearate, microcrystalline cellulose, and talc. The film coating for the 200 mg tablet contains: indigo carmine aluminum lake, polyethylene glycol, polyvinyl alcohol (partly hydrolyzed), talc, and titanium dioxide. The film coating for the 400 mg tablet contains: hypromellose, lactose monohydrate, titanium dioxide, triacetin, and yellow iron oxide. The 200 mg printed tablet also includes black ink which contains: ammonium hydroxide, black iron oxide, isopropyl alcohol, N-butyl alcohol, propylene glycol, and shellac.

12 CLINICAL PHARMACOLOGY

12.1 Mechanism of Action

Sotagliflozin is an inhibitor of SGLT2 and SGLT1. Inhibiting SGLT2 reduces renal reabsorption of glucose and sodium which may influence several physiological functions such as lowering both pre-and afterload of the heart and downregulating sympathetic activity. Inhibiting SGLT1 reduces intestinal absorption of glucose and sodium which likely contributes to diarrhea. The mechanism for sotagliflozin's cardiovascular benefits has not been established.

12.2 Pharmacodynamics

Cardiac Electrophysiology

In a randomized, placebo-controlled, active-comparator, crossover study, 58 healthy subjects were administered a single oral dose of sotagliflozin 800 mg or sotagliflozin 2000 mg (5 times the maximum recommended dose), moxifloxacin, and placebo. No increase in QT corrected for heart rate (QTc) was observed with either 800 mg or 2000 mg sotagliflozin.

12.3 Pharmacokinetics

Plasma Cmax and AUC of sotagliflozin increased in a dose-proportional manner in the therapeutic dose range of 200 mg to 400 mg once daily. Accumulation of sotagliflozin was observed with an approximate 50-100% increase in both Cmax and area under the concentration-time curve from 0 to 24 hours (AUC0-24h) at steady state verses the first day of dosing.

Absorption

The absolute bioavailability of oral sotagliflozin 400 mg dose was approximately 25% (90% confidence interval [CI] 16% to 39%) for area under the concentration-time curve from time 0 to last measurable concentration (AUC0-last). The contribution of enterohepatic circulation to the overall exposure is estimated to be approximately 50%. The median time to maximum plasma concentration (Tmax) ranged from 1.25 to 3 hours, over a single-dose range of 200 mg to 2000 mg. Following administration of multiple doses (400 mg and 800 mg), the median Tmax values ranged from 2.5 to 4 hours.

Food Effect

When sotagliflozin tablets were administered with a high-caloric breakfast compared to fasting conditions, plasma exposure to sotagliflozin as measured by Cmax and AUC0-inf increased by 149% and 50%, respectively. Multiple doses of sotagliflozin 400 mg given immediately before breakfast, 30 minutes prior to breakfast, and 1-hour before breakfast in healthy subjects showed a consistent effect of sotagliflozin on urine glucose excretion (UGE), insulin, and postprandial glucose (PPG) across all dose schedules. It is recommended that INPEFA be taken not more than one hour before the first meal of the day.

Distribution

Both sotagliflozin and its major human metabolite sotagliflozin 3-O-glucuronide exhibited high binding to human plasma proteins in vitro (> 93% bound), which was not dependent on the concentration of sotagliflozin and sotagliflozin 3-O-glucuronide and was not influenced by the degree of renal or hepatic function.

Following administration of a single 400 mg dose of [^14C]-sotagliflozin, the mean blood/plasma ratios for total radioactivity were 0.5 and 0.4 for Cmax and AUC0-last, respectively, and the mean whole blood to plasma concentration ratio of sotagliflozin ranged from 0.5 to 0.6.

The mean apparent volume of distribution of sotagliflozin following administration of a single 400 mg oral dose of [^14C]-sotagliflozin was 9000 L.

Elimination

Metabolism

Following the administration of a single dose of 400 mg [^14C]-sotagliflozin in healthy subjects, sotagliflozin was extensively metabolized predominantly to sotagliflozin 3-O-glucuronide and it represented 94.3% of the radioactivity in plasma.

The key enzymes responsible for the metabolism of sotagliflozin were UGT1A9 and, to a lesser extent, CYP3A4. Following incubation of sotagliflozin with UGT1A9, the 3-O-glucuronide metabolite of sotagliflozin was the main conjugate observed. No acyl glucuronides of sotagliflozin were identified.

Excretion

Following the administration of a single dose of 400 mg [^14C]-sotagliflozin, 57% and 37% of the radioactivity was recovered in the urine and feces, respectively. These results indicate that the main route of elimination was renal. The predominant metabolite detected in urine was sotagliflozin 3-O-glucuronide, representing a mean of 33% of the administered radioactive dose. Unchanged [^14C]-sotagliflozin was the predominant radioactive peak detected in fecal extracts representing a mean of 23% of the total administered radioactive dose. Sotagliflozin undergoes enterohepatic circulation. Following administration of 200 mg and 400 mg, mean terminal half-life (T1/2) ranged from 21 to 35 hours for sotagliflozin and from 19 to 26 hours for sotagliflozin 3-O-glucuronide. Effective half-life of sotagliflozin ranged from 5 to 10 hours. Steady state was generally achieved after 5 days of once daily dosing with sotagliflozin 200 mg and 400 mg.

In healthy volunteers, mean oral clearance (CL/F) of sotagliflozin ranged from 260 to 370 L/hr following administration of 200 mg and 400 mg sotagliflozin. The median population PK model predicted CL/F in type 2 diabetes mellitus patients with normal renal function was about 300 L/hr.

Specific Populations

Renal Impairment

Exposure of sotagliflozin was evaluated in a dedicated PK study in subjects with mild (eGFR 60 to < 90 mL/min/1.73 m²) and moderate (eGFR 30 to < 60 mL/min/1.73 m²) renal impairment and with normal renal function (eGFR ≥ 90 mL/min/1.73 m²). Exposure to sotagliflozin following a single dose of 400 mg was approximately 70% higher in subjects with mild and up to 170% higher in subjects with moderate renal impairment compared to subjects with normal renal function [see Use in Specific Populations (8.6)].

Hepatic Impairment

In a study with subjects with reduced hepatic function, AUC of sotagliflozin was not increased in mild (Child Pugh A) hepatic impaired subjects but was increased by approximately 3-fold in moderate (Child Pugh B) and approximately 6-fold in severe (Child Pugh C) hepatic impaired subjects compared to subjects with normal hepatic function [see Use in Specific Populations (8.7)].

Effects of Age, Sex, Race, and Body Weight on Pharmacokinetics

Based on population PK analysis, age, body weight, sex and race (non-white versus primarily whites) do not have a clinically meaningful effect on the PK of sotagliflozin.

Drug Interactions

In Vitro Studies

The major human metabolite of sotagliflozin, sotagliflozin 3-O-glucuronide, was shown to have an in vitro potential to inhibit CYP3A4 and CYP2D6 and to induce CYP3A4.

Sotagliflozin was shown to have inhibitory effects on P-glycoprotein (P-gp) and breast cancer resistance protein (BCRP). Sotagliflozin is a substrate of the human uptake transporters organic anion transporter (OAT)3, organic-anion-transporting polypeptides (OATP)1B1, and OATP1B3, but not OAT1 and organic cation transporter 2 (OCT2). Sotagliflozin does not inhibit any of these human uptake transporters at clinically relevant plasma concentrations.

In Vivo Studies

Figure 1 summarizes the effect on sotagliflozin by concomitantly administered drugs. The observed changes in overall exposure (AUC) of sotagliflozin following coadministration with hydrochlorothiazide, ramipril, metformin, mefenamic acid, and oral contraceptives are not considered to be clinically relevant. Rifampicin (UGT inducer) decreases exposure to sotagliflozin [see Drug Interactions (7.2)].

Figure 1 Effect of Various Medications on the Pharmacokinetics of Sotagliflozin, Displayed as Geometric Mean AUCs and Cmax Ratios

Vertical reference lines indicate 100% (solid) and the 80%-125% range (dashed)

a400 mg sotagliflozin, administered as a single dose

b400 mg sotagliflozin, at steady state

AUC0-last = area under the concentration-time curve from time 0 to last measurable concentration; AUC0-tau = area under the concentration-time curve from time 0 to end of the dosing period; Cmax = maximum drug concentration; EE = ethinyl estradiol; NO = norgestimate

Figure 2 summarizes the effect on concomitantly administered drugs by sotagliflozin. The increases in exposure (AUC) of metoprolol (CYP2D6 substrate) and rosuvastatin (BCRP substrate), as well as the decrease in exposure to midazolam (CYP3A4 substrate) are not considered to be clinically relevant. The increased exposure (Cmax and AUC) in ramipril is not considered clinically significant because the exposure of ramiprilat, the primary active metabolite, is minimally increased.

The increase in exposure (Cmax and AUC) of digoxin, a P-gp substrate, when coadministered with sotagliflozin, requires monitoring of patients [see Drug Interactions (7.1)].

Figure 2 Effect of Sotagliflozin on the Pharmacokinetics of Various Medications, Displayed as Geometric Mean AUCs and Cmax Ratios

Vertical reference lines indicate 100% (solid) and the 80%-125% range (dashed)

a400 mg sotagliflozin, administered as a single dose

b400 mg sotagliflozin, at steady state

cNorelgestromin is the primary active metabolite of NO

dRamiprilat is the primary active metabolite of ramipril

AUC0-last = area under the concentration-time curve from time 0 to last measurable concentration; AUC0-tau = area under the concentration-time curve from time 0 to end of the dosing period; Cmax maximum drug concentration; EE = ethinyl estradiol; NO = norgestimate

13 NONCLINICAL TOXICOLOGY

13.1 Carcinogenesis, Mutagenesis, Impairment of Fertility

Carcinogenesis

Carcinogenesis was evaluated in a 6-month study in RasH2 transgenic mice and in a 2-year study in Sprague Dawley rats. Sotagliflozin did not increase the incidence of tumors in RasH2 transgenic mice at doses up to 100 mg/kg/day or in rats at doses up to 15-fold (males) and 45-fold (females) clinical exposure at the MRHD.

Mutagenesis

Sotagliflozin was not mutagenic or clastogenic, with or without metabolic activation, in the in vitro Ames bacterial mutagenicity assay, the in vitro Chinese hamster ovary cell chromosomal aberration study, and an in vivo micronucleus assay in rats.

Impairment of Fertility

Sotagliflozin had no effects on mating, fertility, or early embryonic development in treated male or female rats at doses up to 300 mg/kg/day, which represents an exposure multiple of 55 times the human exposure at the MRHD in both males and females.

14 CLINICAL STUDIES

14.1 SOLOIST Study

The SOLOIST (Effects of Sotagliflozin on Clinical Outcomes in Hemodynamically Stable Patients with Type 2 Diabetes Post Worsening Heart Failure) study (NCT03521934) was a randomized, double-blind, placebo-controlled, parallel-group, multicenter study in patients with type 2 diabetes mellitus who had been admitted to the hospital, a heart failure unit, infusion center, or emergency department for worsening heart failure to determine if INPEFA reduces the risk of total occurrence of cardiovascular death, hospitalization for heart failure, and urgent heart failure visit. Patients were randomized to treatment if they met the following criteria for clinical stability: no need for oxygen therapy, a systolic blood pressure of at least 100 mmHg, no need for intravenous inotropic or vasodilator therapy (excluding nitrates) and transitioned from intravenous to oral diuretic therapy.

Of the 1,222 randomized patients, 608 were randomized to INPEFA and 614 to placebo. Assigned treatment was initiated in the hospital or within a median of 2 days following hospital discharge.

The dose of study drug was to be up-titrated from 200 mg to 400 mg sotagliflozin or matching placebo as soon as 2 weeks or up until 8 months after initiation of treatment. The dose was increased to 400 mg once daily for 336 patients (56%) in the sotagliflozin group and 325 patients (53%) in the placebo group. The median time to up-titration was 16 days. Up-titration was to be performed based on the judgment of the investigator, who considered whether the patient's clinical condition was satisfactory, whether the drug was well tolerated, and whether AEs typical of SGLT2 inhibitors had occurred, such as those associated with volume depletion.

At baseline, median age was 70 years, 34% were female, 93% were White and 4% were Black or African American. Median A1C was 7.1%, median body mass index (BMI) was 31 kg/m^2, and median eGFR was 50 mL/min/1.73 m^2. Median left ventricular ejection fraction (LVEF) was 35% (79% with LVEF < 50%), median N-terminal pro B-type natriuretic peptide (NT-proBNP) was 1806 pg/mL, and the median Kansas City Cardiomyopathy Questionnaire-12 (KCCQ-12) score was 41.

At baseline, 86% were treated with at least one antihyperglycemic medication, including 52% with a biguanide, 36% with insulin, 19% with a sulfonylurea, 16% with a dipeptidyl peptidase-4 (DPP4) inhibitor, and 3% with a glucagon-like peptide 1 (GLP-1) receptor agonist. At baseline, 91% were treated with inhibitors of the renin-angiotensin-aldosterone system, 92% with a beta blocker, 95% with a loop diuretic, and 10% with another diuretic.

INPEFA was superior to placebo in reducing the risk of the primary composite endpoint (Hazard Ratio [HR] 0.67 [95% confidence interval (CI) 0.53, 0.85]; p = 0.001). (Table 2).

Table 2 Treatment Effect for the Primary Composite, Components and Secondary Endpoint in the SOLOIST Study
Primary Endpointa | Event Rates per 100 Patient-years |  | Hazard Ratio (95% CI)
Primary Endpointa | INPEFA N = 608 | Placebo N = 614 | Hazard Ratio (95% CI)
Total occurrence of cardiovascular death, hospitalization for heart failure, and urgent heart failure visitb | 51.3 | 76.4 | 0.67 (0.53, 0.85) p = 0.001
Primary Endpoint Components
Cardiovascular deathc,d | 8.4 | 9.4 | 0.84 (0.58, 1.23)
Hospitalization for heart failure | 33.7 | 51.9 | 0.65 (0.49, 0.87)
Urgent heart failure visit | 6.9 | 12.1 | 0.60 (0.34, 1.06)
Secondary Endpointc
Hospitalization for heart failure and urgent heart failure visitc | 40.6 | 63.9 | 0.64 (0.50, 0.84) p = 0.0009
a Based on investigator-reported events in all randomized patients, analyzed according to the treatment group allocated by randomization.
b Predefined primary endpoint.
c Predefined secondary endpoint and tested with multiplicity control.
d Time-to-event analysis was performed; event rates are percentages of patients with events.

Figure 3 displays a cumulative events plot of the primary composite endpoint. The INPEFA and placebo event curves diverged early and remained separated over the study period.

Figure 3 Primary Composite Endpoint (Total Occurrences of Cardiovascular Death, Hospitalization for Heart Failure, and Urgent Heart Failure Visit) Over Time in the SOLOIST Study

Primary composite endpoint was based on investigator-reported events in all randomized patients, analyzed according to the treatment group allocated by randomization.

The results of the primary composite endpoint were generally consistent across prespecified subgroups (Figure 4), including screening LVEF < 50 or ≥ 50% and timing of first dose (post-discharge versus prior to discharge).

Figure 4 Treatment Effect for Primary Composite Endpoint (Total Occurrences of Cardiovascular Death, Hospitalization for Heart Failure, and Urgent Heart Failure Visit) Subgroup Analysis (SOLOIST Study)

HF = heart failure; LVEF = left ventricular ejection fraction; MRA-mineralocorticoid receptor antagonist; NT-proBNP = N-terminal pro B-type natriuretic peptide; PY = patient-years

Primary composite endpoint was based on investigator-reported events in all randomized patients, analyzed according to the treatment group allocated by randomization.

Discharge may have been from hospital or urgent treatment facility where urgent heart failure visit occurred.

Note: The figure above presents effects in various subgroups all of which are baseline characteristics and all of which were pre-specified. The 95% confidence limits that are shown do not take into account how many comparisons were made, nor do they reflect the effect of a particular factor after adjustment for all other factors. Apparent homogeneity or heterogeneity among groups should not be over-interpreted.

14.2 SCORED Study

The SCORED (Effects of Sotagliflozin on Cardiovascular and Renal Events in Patients with Type 2 Diabetes Mellitus, Cardiovascular Risk Factors and Moderately Impaired Renal Function) study (NCT03315143) was a randomized, double-blind, placebo-controlled, parallel-group, multicenter study in patients with type 2 diabetes mellitus (A1C > 7%), chronic kidney disease (eGFR 25 to 60 mL/min/1.73 m^2), and additional cardiovascular risk factors, such as a history of heart failure, obesity, dyslipidemia, hypertension, or elevated cardiac and inflammatory biomarkers, to determine if INPEFA reduces the risk of total occurrence of cardiovascular death, hospitalization for heart failure, and urgent heart failure visit. Of the 10,584 randomized patients, 5,292 were randomized to INPEFA and 5,292 to placebo.

The dose of study drug was to be up-titrated from 200 mg to 400 mg sotagliflozin or matching placebo as soon as 4 weeks or up until 6 months after initiation of treatment. The dose was increased to 400 mg once daily for 3,934 patients (74%) in the INPEFA group and for 3,987 patients (75%) in the placebo group. The median time to up-titration was 29 days. Up-titration was to be performed based on the judgment of the investigator, who considered whether the patient's clinical condition was satisfactory, whether the drug was well tolerated, and whether AEs typical of SGLT2 inhibitors had occurred, such as those associated with volume depletion.

At baseline, median age was 68 years, 45% were female, 82% were White, 3% Black or African American, 6% Asian, and 4% American Indian or Native Alaskan. Median A1C was 8.3%, median BMI was 32 kg/m^2, median eGFR was 45 mL/min/1.73 m^2 (8% with eGFR < 30, 44% with eGFR 30 to < 45, and 48% with eGFR ≥ 45 mL/min/1.73 m^2), and median urinary albumin-to-creatinine ratio (UACR) was 82 mg/g (32% with UACR ≥ 300 mg/g). A history of heart failure was present in 31%, prior myocardial infarction had occurred in 20%, a prior cerebrovascular event had occurred in 9%, and coronary revascularization had been performed in 22% of patients prior to study entry.

At baseline, 97% were treated with at least one antihyperglycemic medication, including 56% with a biguanide, 64% with insulin, 27% with a sulfonylurea, 20% with a DPP4 inhibitor, and 6% with a GLP-1 receptor agonist. At baseline, 88% were treated with inhibitors of the renin-angiotensin-aldosterone system, 14% with a beta blocker, 42% with a calcium channel blocker, 35% with a loop diuretic, and 30% with another diuretic.

INPEFA was superior to placebo in reducing the risk of the primary composite endpoint (HR 0.75 [95% CI 0.63, 0.88]; p < 0.001) (Table 3).

Table 3 Treatment Effect for the Primary Composite, Components and Secondary Endpoint in the SCORED Study
Primary Endpointa | Event Rates (per 100 Patient-years) |  | Hazard Ratio (95% CI)
Primary Endpointa | INPEFA N = 5,292 | Placebo N = 5,292 | Hazard Ratio (95% CI)
Total occurrence of cardiovascular death, hospitalization for heart failure, and urgent heart failure visitb | 5.6 | 7.5 | 0.75 (0.63, 0.88) p < 0.001
Primary Endpoint Components
Cardiovascular deathc,d | 2.9 | 3.2 | 0.90 (0.73, 1.12)
Hospitalization for heart failure | 2.8 | 4.2 | 0.66 (0.53, 0.82)
Urgent heart failure visit | 0.7 | 0.9 | 0.73 (0.48, 1.11)
Secondary Endpointc
Hospitalization for heart failure or urgent heart failure visitc | 3.5 | 5.1 | 0.67 (0.55, 0.82) p = 0.0001
a Based on investigator-reported events in all randomized patients, analyzed according to the treatment group allocated by randomization.
b Predefined primary endpoint.
c Predefined secondary endpoint and tested with multiplicity control.
d Time-to-event analysis was performed; event rates are percentages of patients with events.

Figure 5 displays a cumulative events plot of the primary composite endpoint. The INPEFA and placebo event curves separated early and continued to diverge over the study period following randomization.

Figure 5 Primary Composite Endpoint (Total Occurrences of Cardiovascular Death, Hospitalization for Heart Failure, and Urgent Heart Failure Visit) Over Time in the SCORED Study

Primary composite endpoint was based on investigator-reported events in all randomized patients, analyzed according to the treatment group allocated by randomization.

The results of the primary composite endpoint were generally consistent across prespecified subgroups, including history of cardiovascular disease, history of heart failure, and screening LVEF < 50 or ≥ 50% (Figure 6).

Figure 6 Treatment Effect for Primary Composite Endpoint (Total Occurrences of Cardiovascular Death, Hospitalization for Heart Failure, and Urgent Heart Failure Visit) Subgroup Analysis (SCORED Study)

CVD = cardiovascular disease; eGFR = estimated glomerular filtration rate; LVEF = left ventricular ejection fraction; HF = heart failure; PY = patient-years

Primary composite endpoint was based on investigator-reported events in all randomized patients, analyzed according to the treatment group allocated by randomization.

Note: The figure above presents effects in various subgroups all of which are baseline characteristics and all of which were pre-specified. The 95% confidence limits that are shown do not take into account how many comparisons were made, nor do they reflect the effect of a particular factor after adjustment for all other factors. Apparent homogeneity or heterogeneity among groups should not be over-interpreted.

16 HOW SUPPLIED/STORAGE AND HANDLING

INPEFA tablets are oval and film-coated.

 |  | Printed Tablets |  | Debossed Tablets
Strength (mg) | Color | Printing | Bottle/30 | Deboss | Bottle/30 | Blister/30 (3 x 10)
200 | Blue | LX200 on one side | NDC 70183-220-30 | LEX on one side, 200 on other side | NDC 70183-221-30 | NDC 70183-221-31
400 | Yellow | -- | -- | LEX on one side, 400 on other side | NDC 70183-241-30 | --

Storage

Store at 20°C to 25°C (68°F to 77°F); excursions permitted between 15°C and 30°C (59°F and 86°F) [see USP Controlled Room Temperature].

17 PATIENT COUNSELING INFORMATION

Advise the patient to read the FDA-approved patient labeling (Medication Guide).

Risk of Diabetic Ketoacidosis in Patients with Type 1 Diabetes Mellitus and Other Ketoacidosis

In patients with type 1 diabetes mellitus, inform them that using INPEFA can increase their risk of life-threatening diabetic ketoacidosis. For all other patients, inform them that INPEFA can cause potentially fatal ketoacidosis and that type 2 diabetes mellitus is a risk factor.

Educate all patients on precipitating factors (such as infection, reduced caloric intake, ketogenic diet, surgery, insulin dose reduction, dehydration, and alcohol abuse) and symptoms of ketoacidosis (including nausea, vomiting, abdominal pain, tiredness, and labored breathing). Inform patients that blood glucose may be normal even in the presence of ketoacidosis.

Advise patients that they may be asked to monitor ketones. If symptoms of ketoacidosis occur, instruct patients to discontinue INPEFA and seek medical attention immediately [see Warnings and Precautions (5.1)].

Volume Depletion

Inform patients that symptomatic hypotension may occur with INPEFA and advise them to contact their healthcare provider if they experience such symptoms [see Warnings and Precautions (5.2)]. Inform patients that dehydration may increase the risk for hypotension, and to have adequate fluid intake.

Serious Urinary Tract Infections

Inform patients of the potential for urinary tract infections, which may be serious. Provide them with information on the symptoms of urinary tract infections. Advise them to seek medical advice promptly if such symptoms occur [see Warnings and Precautions (5.3)].

Hypoglycemia with Concomitant Use with Insulin and Insulin Secretagogues

Inform patients that the incidence of hypoglycemia is increased when INPEFA is used in combination with insulin and that a lower dose of insulin may be required to reduce the risk of hypoglycemia [see Warnings and Precautions (5.4)].

Necrotizing Fasciitis of the Perineum (Fournier's Gangrene)

Inform patients that necrotizing infections of the perineum (Fournier's Gangrene) have occurred with INPEFA in patients with diabetes mellitus. Counsel patients to promptly seek medical attention if they develop pain, tenderness, redness, or swelling of the genitals or the area from the genitals back to the rectum, along with a fever above 100.4°F or malaise [see Warnings and Precautions (5.5)].

Genital Mycotic Infections in Females (e.g., Vulvovaginitis)

Inform female patients that vaginal yeast infections may occur and provide them with information on the signs and symptoms of vaginal yeast infections. Advise them of treatment options and when to seek medical advice [see Warnings and Precautions (5.6)].

Genital Mycotic Infections in Males (e.g., Balanitis)

Inform male patients that yeast infections of the penis (e.g., balanitis or balanoposthitis) may occur, especially in patients with prior history. Provide them with information on the signs and symptoms of balanitis and balanoposthitis (rash or redness of the glans or foreskin of the penis). Advise them of treatment options and when to seek medical advice [see Warnings and Precautions (5.6)].

Hypersensitivity Reactions

Inform patients that hypersensitivity reactions (e.g., urticaria, anaphylactic reactions, and angioedema) have been reported with other SGLT2 inhibitors. Advise patients to immediately report any signs or symptoms suggesting allergic reaction or angioedema and to discontinue the drug until they have consulted their prescribing physician.

Pregnancy

Advise pregnant patients of the potential risk to a fetus with treatment with INPEFA.

Instruct patients to immediately inform their healthcare provider if pregnant or planning to become pregnant [see Use in Specific Populations (8.1)].

Lactation

Advise patients that use of INPEFA is not recommended while breastfeeding [see Use in Specific Populations (8.2)].

Laboratory Tests

Due to its mechanism of action, patients taking INPEFA will test positive for glucose in their urine.

Missed Dose

If a dose of INPEFA is missed by more than 6 hours, take the next dose as prescribed the next day. Advise patients not to take two doses of INPEFA at the same time.

Manufactured for:
Lexicon Pharmaceuticals, Inc. (The Woodlands, TX 77381)

INPEFA is a registered trademark of Lexicon Pharmaceuticals, Inc.

MEDICATION GUIDE
INPEFA® (in peh' fah)
(sotagliflozin)
tablets, for oral use

What is the most important information I should know about INPEFA?
INPEFA can cause serious side effects, including:

- Ketoacidosis (acidic blood with increased ketones in your blood or urine). Ketoacidosis has happened in people who have type 1 or type 2 diabetes during treatment with INPEFA. Ketoacidosis can happen with INPEFA even if your blood sugar is not high. Your healthcare provider may ask you to periodically check ketones in your urine or blood. Ketoacidosis can also happen in people who are sick or who have surgery during treatment with INPEFA. Ketoacidosis is a serious condition which needs to be treated in a hospital. Ketoacidosis may lead to death.
  - Stop taking INPEFA and call your healthcare provider or get medical help right away if you get any of the following symptoms. If possible, check for ketones in your urine or blood, even if your blood sugar is less than 250 mg/dL:
    - nausea
    - vomiting
    - trouble breathing
    - stomach-area (abdominal) pain
    - tiredness
    - ketones in your urine or blood
- Dehydration. INPEFA can cause some people to become dehydrated (the loss of body water and salt). Dehydration may cause you to feel dizzy, faint, lightheaded, or weak, especially when you stand up (orthostatic hypotension). There have been reports of sudden kidney injury due to dehydration in people with type 2 diabetes who are taking a medicine that works like INPEFA.
  You may be at higher risk of dehydration if you:
  - take medicines to lower your blood pressure, including water pills (diuretics)
  - are 65 years of age or older
  - are on a low salt diet
  - have kidney problems
  Talk to your healthcare provider about what you can do to prevent dehydration including how much fluid you should drink on a daily basis. Call your healthcare provider right away if you reduce the amount of food or liquid you drink, for example if you cannot eat or you start to lose liquids from your body, for example from vomiting, diarrhea, or being in the sun too long.

See “What are the possible side effects of INPEFA?” for more information about side effects.

What is INPEFA?
INPEFA is a prescription medicine used to reduce the risk of death due to heart problems (cardiovascular death), hospitalization for heart failure, and urgent visits to the doctor for heart failure in adults with:

- heart failure (when the heart is weak and cannot pump enough blood to the rest of your body), or
- type 2 diabetes, chronic kidney disease, and other cardiovascular risk factors.

It is not known if INPEFA is safe and effective in children under 18 years of age.

Do not take INPEFA if you:

- are allergic to sotagliflozin or any of the ingredients in INPEFA. See the end of this Medication Guide for a list of ingredients in INPEFA. Symptoms of a serious allergic reaction to INPEFA may include:
  - skin rash
  - raised red patches on your skin (hives)
  - swelling of the face, lips, tongue, and throat that may cause difficulty in breathing or swallowing
  If you have any of these symptoms, stop taking INPEFA and call your healthcare provider or go to the nearest hospital emergency room right away.

Before taking INPEFA, tell your healthcare provider about all of your medical conditions, including if you:

- have type 1 diabetes or have had diabetic ketoacidosis.
- are going to have surgery or a procedure that requires fasting. Your healthcare provider may stop your INPEFA for at least 3 days before you have surgery. Talk to your healthcare provider if you are having surgery about when to stop taking INPEFA and when to start it again.
- are eating less or there is a change in your diet.
- have or have had problems with your pancreas, including pancreatitis or surgery on your pancreas.
- drink alcohol very often or drink a lot of alcohol over a short period (“binge” drinking).
- have a history of urinary tract infections or problems urinating.
- have a history of infection of the vagina or penis.
- have kidney or liver problems.
- are pregnant or plan to become pregnant. INPEFA may harm your unborn baby. Tell your healthcare provider right away if you become pregnant during treatment with INPEFA. Your healthcare provider may switch you to a different medicine.
- are breastfeeding or plan to breastfeed. It is not known if INPEFA passes into your breast milk. Talk to your healthcare provider about the best way to feed your baby during treatment with INPEFA. You should not breastfeed during treatment with INPEFA.

Tell your healthcare provider about all the medicines you take, including prescription and over-the-counter medicines, vitamins, and herbal supplements. INPEFA may affect the way other medicines work, and other medicines may affect how INPEFA works.

How should I take INPEFA?

- Take INPEFA exactly as your healthcare provider tells you to take it.
- Do not change your dose of INPEFA without talking to your healthcare provider.
- Take INPEFA by mouth 1 time each day no more than 1 hour before your first meal of the day.
- Swallow INPEFA tablets whole. Do not cut, crush, or chew.
- If you miss a dose of INPEFA by more than 6 hours after taking INPEFA, take your next dose at your next scheduled time the next day.
- INPEFA will cause your urine to test positive for glucose.
- Your healthcare provider may do certain blood tests before you start INPEFA and during your treatment as needed.
- If you take too much INPEFA, call your healthcare provider or local poison control center, or go to the nearest emergency room right away.

What are the possible side effects of INPEFA?
INPEFA can cause serious side effects, including:

- See “What is the most important information I should know about INPEFA?”
- Serious urinary tract infections. Serious urinary tract infections that may lead to hospitalization have happened in people who are taking INPEFA. Tell your healthcare provider if you have any signs or symptoms of a urinary tract infection such as a burning feeling when passing urine, a need to urinate often, the need to urinate right away, pain in the lower part of your stomach (pelvis), or blood in the urine. Sometimes people also may have a fever, back pain, nausea, or vomiting.
- Low blood sugar (hypoglycemia). If you take INPEFA with another medicine that can cause low blood sugar, such as a sulfonylurea or insulin, your risk of getting low blood sugar is higher. The dose of your sulfonylurea medicine or insulin may need to be lowered while you take INPEFA. Signs and symptoms of low blood sugar may include:
  - headache
  - shaking or feeling jittery
  - irritability
  - fast heartbeat
  - weakness
  - drowsiness
  - sweating
  - confusion
  - dizziness
  - hunger
- A rare but serious bacterial infection that causes damage to the tissue under the skin (necrotizing fasciitis) in the area between and around the anus and genitals (perineum). Necrotizing fasciitis of the perineum has happened in women and men with diabetes who take INPEFA. Necrotizing fasciitis of the perineum may lead to hospitalization, may require multiple surgeries, and may lead to death. Seek medical attention immediately if you have a fever or you are feeling very weak, tired, or uncomfortable (malaise) and you develop any of the following symptoms in the area between and around the anus and genitals:
  - pain or tenderness
  - swelling
  - redness of skin (erythema)
- Vaginal yeast infection. Symptoms of a vaginal yeast infection include:
  - vaginal odor
  - white or yellowish vaginal discharge (discharge may be lumpy or look like cottage cheese)
  - vaginal itching
- Yeast infection of the penis (balanitis or balanoposthitis). Swelling of an uncircumcised penis may develop that makes it difficult to pull back the skin around the tip of the penis. Other symptoms of yeast infection of the penis include:
  - redness, itching, or swelling of the penis
  - rash of the penis
  - foul smelling discharge from the penis
  - pain in the skin around the penis

Talk to your healthcare provider about what to do if you get symptoms of a yeast infection of the vagina or penis. Your healthcare provider may suggest you use an over-the-counter antifungal medicine. Talk to your healthcare provider right away if you use an over-the-counter antifungal medication and your symptoms do not go away.
The most common side effects of INPEFA include:

  - urinary tract infection
  - dehydration
  - diarrhea
  - low blood sugar levels

These are not all the possible side effects of INPEFA. For more information, ask your healthcare provider or pharmacist.
Call your doctor for medical advice about side effects. You may report side effects to FDA at 1-800-FDA-1088.

How should I store INPEFA?

- Store INPEFA at room temperature between 68°F to 77°F (20°C to 25°C).

Keep INPEFA and all medicines out of the reach of children.

General information about the safe and effective use of INPEFA.
Medicines are sometimes prescribed for purposes other than those listed in a Medication Guide. Do not use INPEFA for a condition for which it is not prescribed. Do not give INPEFA to other people, even if they have the same symptoms you have. It may harm them. You can ask your pharmacist or healthcare provider for information about INPEFA that is written for health professionals.

What are the ingredients in INPEFA?
Active ingredient: sotagliflozin.
Inactive ingredients: The core of the tablet contains: colloidal silicon dioxide, croscarmellose sodium, magnesium stearate, microcrystalline cellulose, and talc. The film coating for the 200 mg tablet contains: indigo carmine aluminum lake, polyethylene glycol, polyvinyl alcohol (partly hydrolyzed), talc, and titanium dioxide. The film coating for the 400 mg tablet contains: hypromellose, lactose monohydrate, titanium dioxide, triacetin, and yellow iron oxide. For tablets that are printed and not debossed, the ink contains: ammonium hydroxide, black iron oxide, isopropyl alcohol, N-butyl alcohol, propylene glycol, and shellac.
Manufactured for: Lexicon Pharmaceuticals, Inc. The Woodlands, TX, 77381.
INPEFA is a registered trademark of Lexicon Pharmaceuticals, Inc.
For more information about INPEFA, go to www.lexpharma.com or call 1-855-330-2573.

This Medication Guide has been approved by the U.S. Food and Drug Administration.

Issued 01/2024

PACKAGE LABEL

Principal Display Panel – 30 Count 200 mg Bottle Label

NDC 70183-220-30

XXXXXXXX

inpefa™

sotagliflozin tablets

Rx only

200 mg

Dispense with Enclosed
Medication Guide

30 Tablets for oral use

Lexicon
pharmaceuticals

PACKAGE LABEL

Principal Display Panel – 30 Count 200 mg Bottle Label

NDC 70183-221-30

2000015930

Rx only

inpefa™

sotagliflozin tablets

200 mg

Dispense with Enclosed
Medication Guide

30 Tablets for oral use

Lexicon
pharmaceuticals

PACKAGE LABEL

Principal Display Panel – 30 Count 400 mg Bottle Label

NDC 70183-241-30

2000015933

Rx only

inpefa™

sotagliflozin tablets

400 mg

Dispense with Enclosed Medication Guide

30 Tablets for oral use

Lexicon
pharmaceuticals

PACKAGE LABEL

Principal Display Panel – 30 Count 400 mg Bottle Label

NDC 70183-240-30

XXXXXXXX

inpefa™

sotagliflozin tablets

Rx only

400 mg

Dispense with Enclosed Medication Guide

30 Tablets for oral use

Lexicon
pharmaceuticals